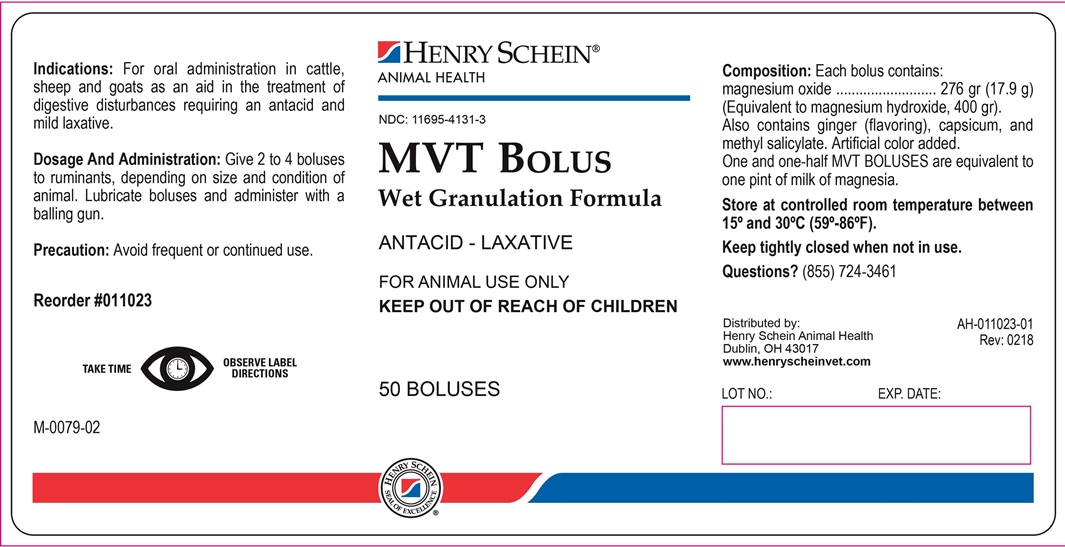 DRUG LABEL: MVT Bolus
NDC: 11695-4131 | Form: TABLET
Manufacturer: Henry Schein Animal Health
Category: animal | Type: OTC ANIMAL DRUG LABEL
Date: 20180227

ACTIVE INGREDIENTS: MAGNESIUM OXIDE 17.9 g/1 1
INACTIVE INGREDIENTS: SODIUM STARCH GLYCOLATE TYPE A CORN; MAGNESIUM STEARATE; STARCH 1500, PREGELATINIZED; WATER

MVT Bolus

INDICATIONS AND USAGE

Wet Granulation Formula

ANTACID - LAXATIVE

FOR ANIMAL USE ONLY

KEEP OUT OF REACH OF CHILDREN

Indications:

For oral administration in cattle, sheep and goats as a aid in the treatment of digestive disturbances requiring and antacid and mild laxative.

Dosage And Administration

Give 2 to 4 boluses to ruminants, depending on size and condition of animal. Lubricate boluses and administer with a balling gun.

Precaution

Avoid frequent or continued use.

Composition

Each bolus contains:

magnesium oxide ......................... 276 gr (17.9 g)

(Equivalent to magnesium hydroxide3, 400 gr.).

Also contains ginger (flavoring), capsicum, and methyl salicylate. Artificial color added.

One and one-half MVT BOLUSES are equivalent to one pint of milk of magnesia.

STORAGE AND HANDLING

Store at controlled room temperature between 15° and 30°C (59°-86°F).

Keep tightly closed when not in use.